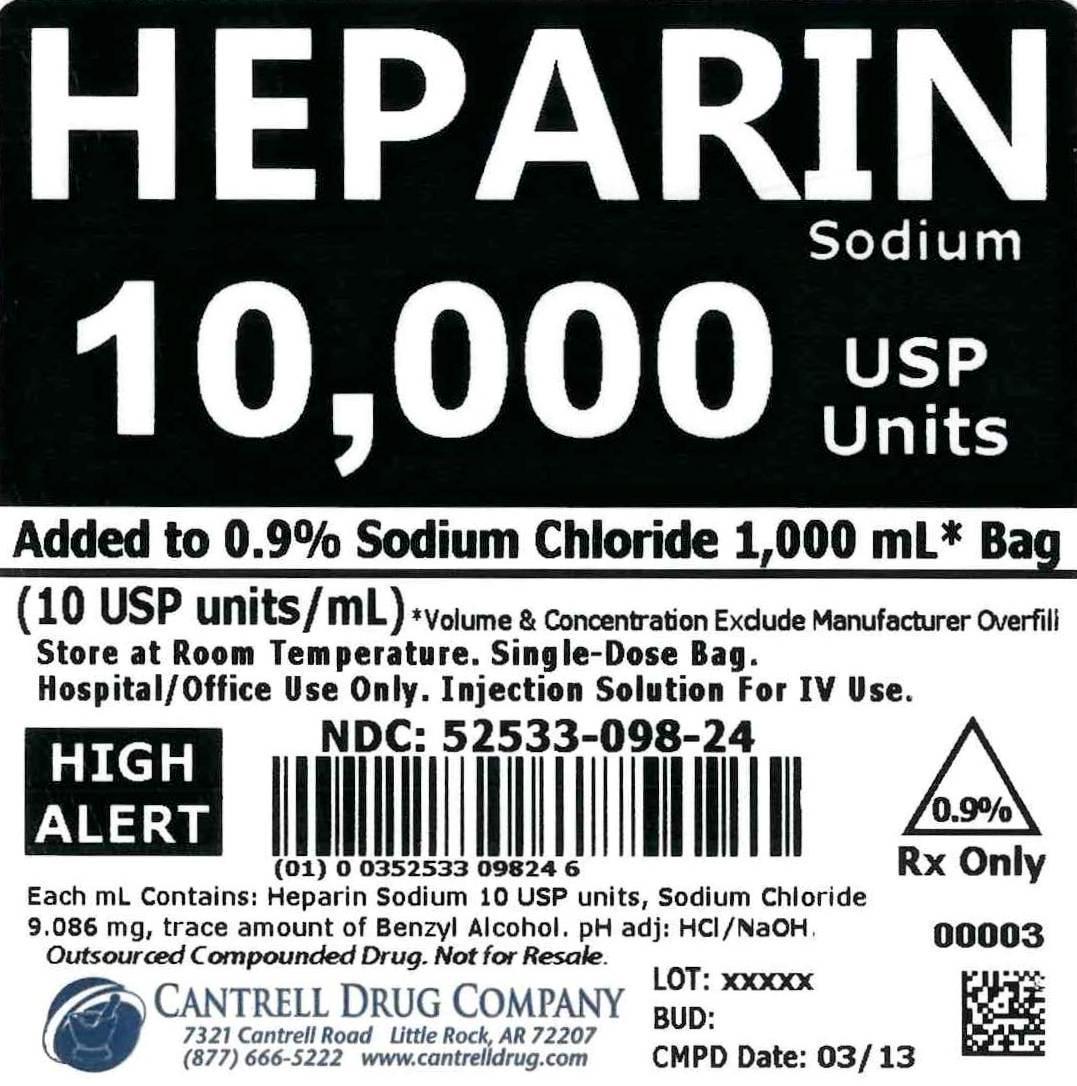 DRUG LABEL: Heparin Sodium
NDC: 52533-098 | Form: INJECTION, SOLUTION
Manufacturer: Cantrell Drug Company
Category: prescription | Type: HUMAN PRESCRIPTION DRUG LABEL
Date: 20150112

ACTIVE INGREDIENTS: Heparin Sodium 10 [USP'U]/1 mL
INACTIVE INGREDIENTS: Sodium Chloride 9 mg/1 mL; BENZYL ALCOHOL 0.0001 mL/1 mL; Water

Heparin Sodium 10,000 USP Units Added to 0.9% Sodium Chloride 1,000 mL Bag